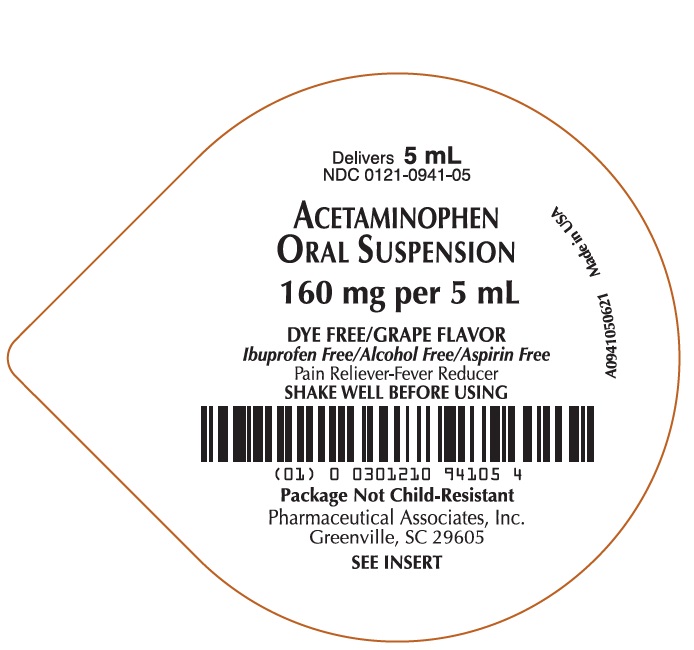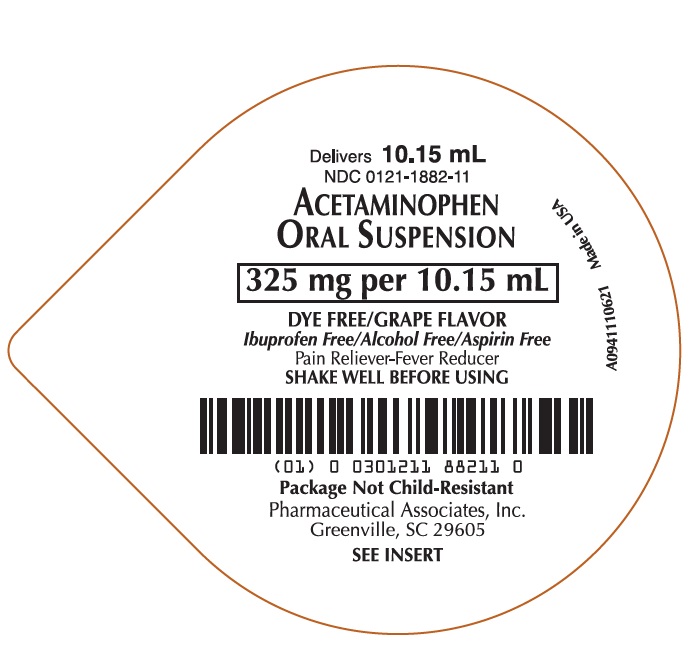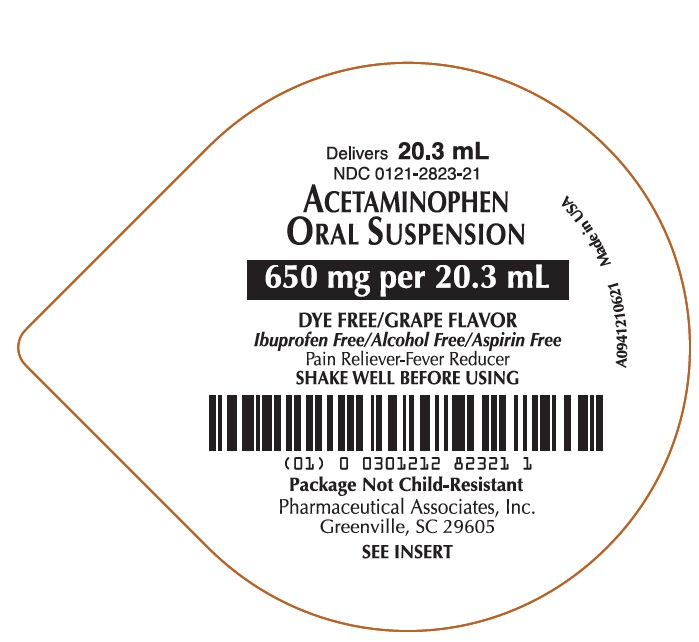 DRUG LABEL: Acetaminophen
NDC: 0121-0941 | Form: SUSPENSION
Manufacturer: PAI Holdings, LLC dba PAI Pharma
Category: otc | Type: HUMAN OTC DRUG LABEL
Date: 20250818

ACTIVE INGREDIENTS: ACETAMINOPHEN 160 mg/5 mL
INACTIVE INGREDIENTS: ACESULFAME POTASSIUM; BUTYLPARABEN; ANHYDROUS CITRIC ACID; GLYCERIN; HIGH FRUCTOSE CORN SYRUP; POLYSORBATE 80; PROPYLENE GLYCOL; WATER; SODIUM BENZOATE; SORBITOL SOLUTION; XANTHAN GUM

Acetaminophen Oral Suspension

Drug Facts

Active ingredient (in each 5 mL)

Acetaminophen 160 mg

Purpose

Pain reliever/fever reducer

Uses

temporarily:

- reduces fever
- relieves minor aches and pains due to:
  - the common cold
  - flu
  - headache
  - sore throat
  - toothache

Warnings

Liver warning

This product contains acetaminophen. Severe liver damage may occur if

- adult takes more than 4,000 mg of acetaminophen in 24 hours
- child takes more than 5 doses in 24 hours
- taken with other drugs containing acetaminophen
- adult has 3 or more alcoholic drinks every day while using this product

Allergy alert

Acetaminophen may cause severe skin reactions. Symptoms may include:

- skin reddening
- blisters
- rash

If a skin reaction occurs, stop use and seek medical help right away.

Sore throat warning

If sore throat is severe, persists for more than 2 days, is accompanied or followed by fever, headache, rash, nausea, or vomiting, consult a doctor promptly.

Do not use

- with any other drug containing acetaminophen (prescription or nonprescription). If you are not sure whether a drug contains acetaminophen, ask a doctor or pharmacist.
- if you have ever had an allergic reaction to this product or any of its ingredients

Ask a doctor before use if the user has liver disease

Ask a doctor or pharmacist before use if the user is taking the blood thinning drug warfarin

When using this product do not exceed recommended dose (see overdose warning)

Stop use and ask a doctor if

- pain gets worse or lasts more than 10 days (for adults) or 5 days (for children)
- fever gets worse or lasts more than 3 days
- new symptoms occur
- redness or swelling is present

These could be signs of a serious condition.

- do not give this product to children for the pain of arthritis unless directed by a doctor

PREGNANCY OR BREAST FEEDING

If pregnant or breast-feeding, ask a health professional before use.

Keep out of reach of children.

Overdose warning

In case of overdose, get medical help or contact a Poison Control Center right away (1-800-222-1222). Quick medical attention is critical for adults as well as for children even if you do not notice any signs or symptoms.

Directions

- Use as directed per healthcare professional.
- do not take more than directed (see overdose warning)
- shake well before using
- find the right dose on chart below. If possible, use weight to dose; otherwise, use age.
- repeat dose every 4 hours while symptoms last
- do not take more than 5 times in 24 hours

Weight (lb) | Age (yr) | Dose (mL) [or as directed by a doctor]
Under 24 | Under 2 years | ask a doctor
24-35 | 2-3 years | 5 mL
36-47 | 4-5 years | 7.5 mL
48-59 | 6-8 years | 10 mL
60-71 | 9-10 years | 12.5 mL
72-95 | 11 years | 15 mL
Over 96 | adults and children 12 years and over | 20 mL

Other information

- each 5 mL contains: sodium: 2 mg
- Store at 20° to 25°C (68° to 77°F)

Inactive ingredients

acesulfame potassium, butylparaben, citric acid anhydrous, flavoring, glycerin, high fructose corn syrup, polysorbate 80, propylene glycol, purified water, sodium benzoate, sorbitol solution, and xanthan gum.

Alcohol Free, Aspirin Free, Gluten Free, Ibuprofen Free

How Supplied

- grape flavored suspension supplied in the following oral dosage forms:

NDC 0121-0941-05: 5 mL unit dose cup, in a tray of ten cups.

NDC 0121-1882-11: 10.15 mL unit dose cup, in a tray of ten cups.

NDC 0121-2823-21: 20.3 mL unit dose cup, in a tray of ten cups.

QUESTIONS

Call 1-800-845-8210.

MANUFACTURED BY

Pharmaceutical Associates, Inc.

Greenville, SC 29860

www.paipharma.com

PRINCIPAL DISPLAY PANEL - 5 mL Cup Label

NDC 0121-0941-05

ACETAMINOPHEN ORAL SUSPENSION

160 mg per 5 mL

DYE FREE/GRAPE FLAVOR

Ibuprofen Free/Alcohol Free/Aspirin Free

Pain Reliever-Fever Reducer

SHAKE WELL BEFORE USING

Package Not Child-Resistant

Pharmaceutical Associates, Inc.

Greenville, SC 29605

PRINCIPAL DISPLAY PANEL - 10.15 mL Cup Label

NDC 0121-1882-11

ACETAMINOPHEN ORAL SUSPENSION

325 mg per 10.15 mL

DYE FREE/GRAPE FLAVOR

Ibuprofen Free/Alcohol Free/Aspirin Free

Pain Reliever-Fever Reducer

SHAKE WELL BEFORE USING

Package Not Child-Resistant

Pharmaceutical Associates, Inc.

Greenville, SC 29605

PRINCIPAL DISPLAY PANEL - 20.3 mL Cup Label

NDC 0121-2823-21

ACETAMINOPHEN ORAL SUSPENSION

650 mg per 20.3 mL

DYE FREE/GRAPE FLAVOR

Ibuprofen Free/Alcohol Free/Aspirin Free

Pain Reliever-Fever Reducer

SHAKE WELL BEFORE USING

Package Not Child-Resistant

Pharmaceutical Associates, Inc.

Greenville, SC 29605